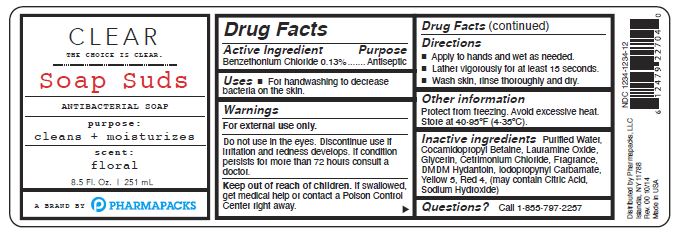 DRUG LABEL: CLEAR S Suds
NDC: 73599-003 | Form: SOLUTION
Manufacturer: PHARMAPACKS, LLC
Category: otc | Type: HUMAN OTC DRUG LABEL
Date: 20200306

ACTIVE INGREDIENTS: BENZETHONIUM CHLORIDE 0.13 g/100 mL
INACTIVE INGREDIENTS: FD&C YELLOW NO. 5; FD&C RED NO. 4; WATER; COCAMIDOPROPYL BETAINE; LAURAMINE OXIDE; GLYCERIN; CETRIMONIUM CHLORIDE; IODOPROPYNYL BUTYLCARBAMATE; SODIUM HYDROXIDE; CITRIC ACID MONOHYDRATE; DMDM HYDANTOIN

Active Ingredient

Benzethonium Chloride 0.13%

Purpose

Antiseptic

Uses

- For handwashing to decrease bacteria on the skin.

Warnings

For external use only.

Do not use in the eyes.

Discontinue use if irritation and redness develops.

If condition persists for more than 72 hours consult a doctor.

Keep out of reach of children.

If swallowed, get medical help or contact a Poison Control Center right away.

Directions

- Apply to hands and wet as needed.
- Lather vigorously for at least 15 seconds.
- Wash skin, rinse thoroughly and dry.

Other information

Protect from freezing.

Avoid excessive heat.

Store at 40-95 F (4-35 C).

Inactive ingredients

Purified Water, Cocamidopropyl Betaine, Laramine Oxide, Glycerin, Cetrimonim Chloride, Fragrance, DMDM Hydantoin, Iodopropynyl Carbamate, Yellow 6, Red 4, (may contain Citric Acid, Sodium Hydroxide)

Questions?

Call 1-855-797-2257

PACKAGE LABEL

CLEAR

The Choice Is Clear

SOAP SUDS

Antibacterial Soap

purpose:

cleans + moisturizes

scent:

floral

8.5 Fl.Oz. 125mL

A Brand By PHARMAPACKS